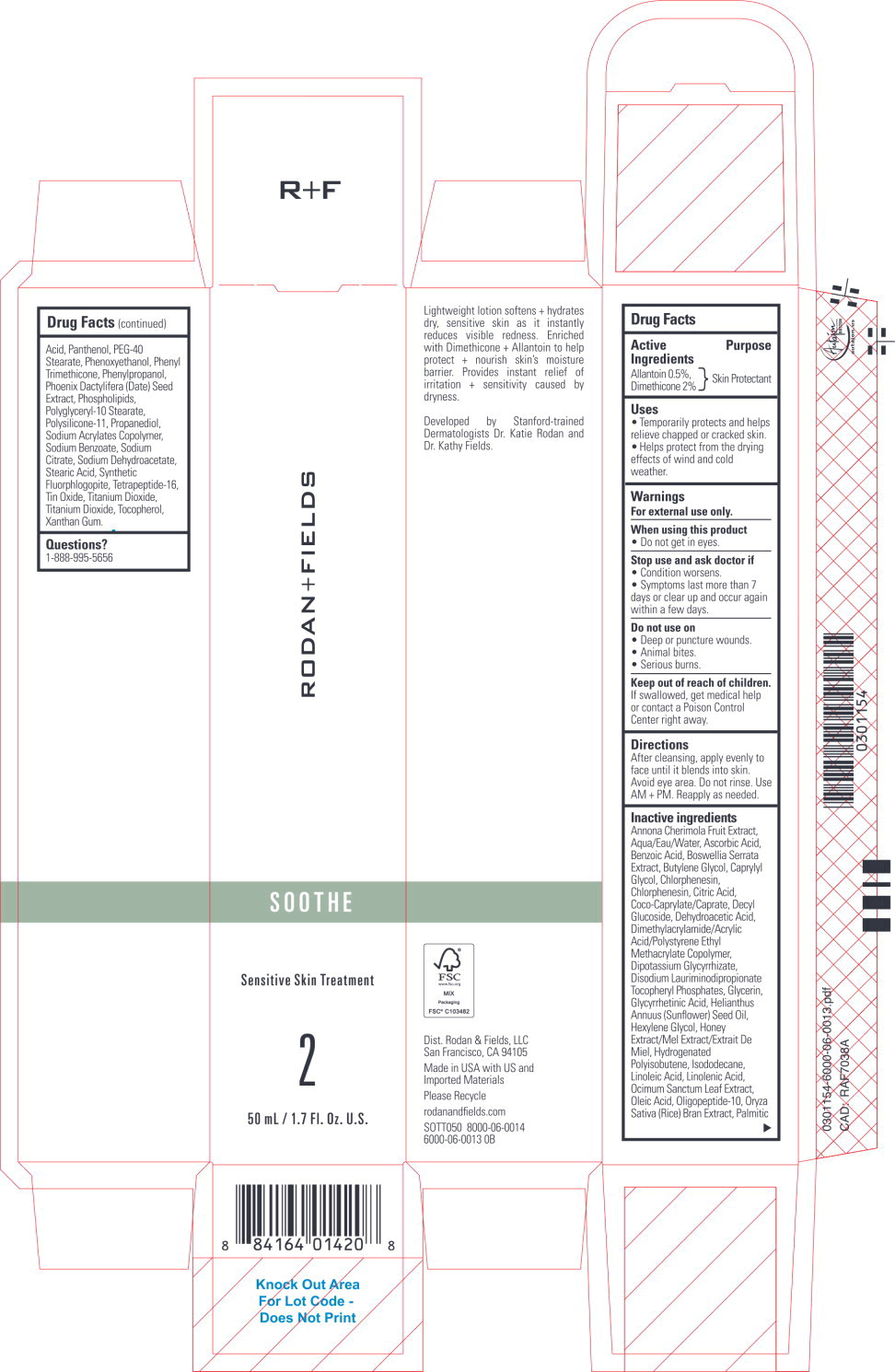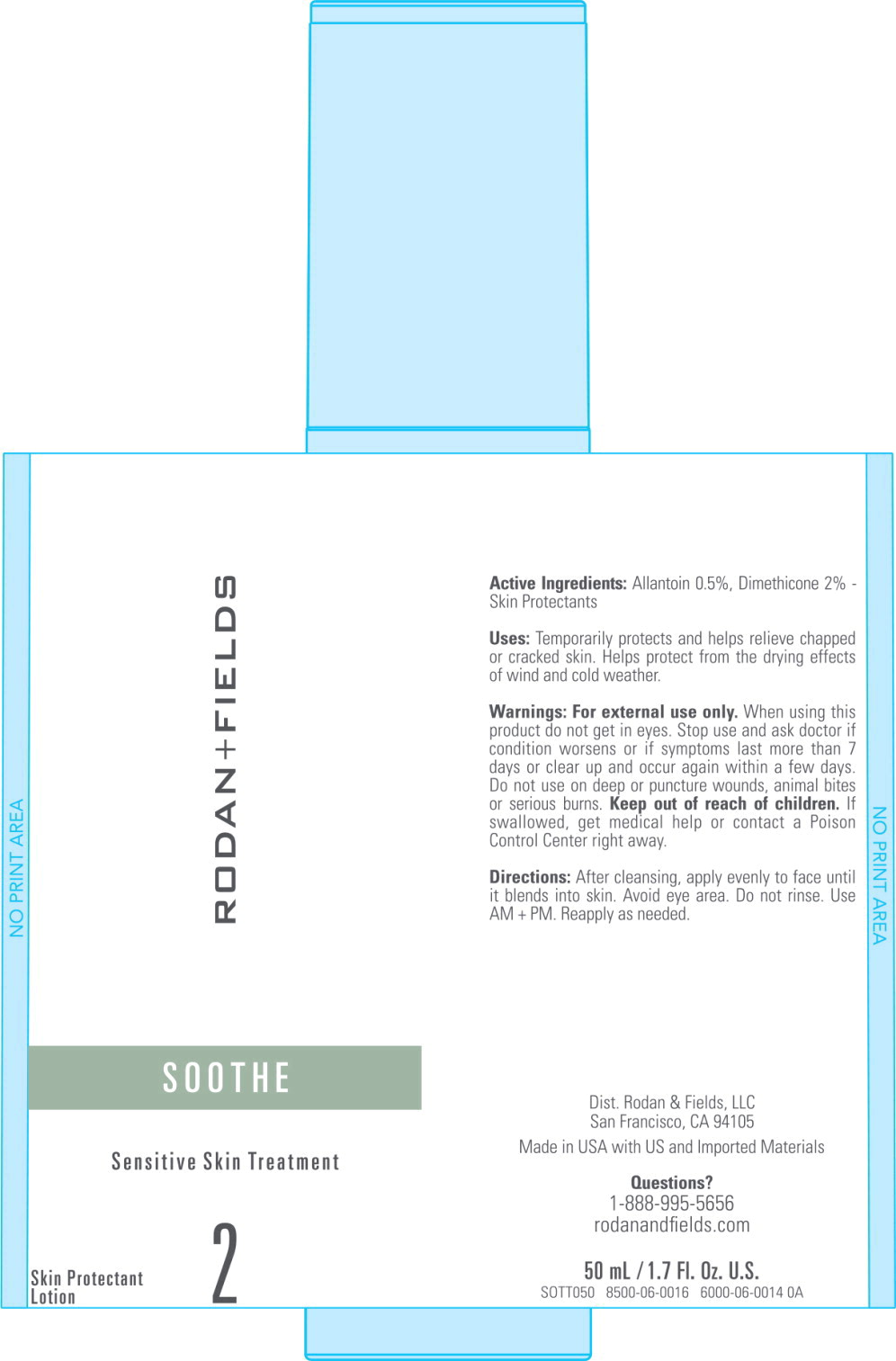 DRUG LABEL: SOOTHE Sensitive Skin Treatment
NDC: 14222-2420 | Form: LOTION
Manufacturer: Rodan & Fields
Category: otc | Type: HUMAN OTC DRUG LABEL
Date: 20241209

ACTIVE INGREDIENTS: Allantoin 0.5 g/100 mL; Dimethicone 2 g/100 mL
INACTIVE INGREDIENTS: CHERIMOYA; ASCORBIC ACID; BENZOIC ACID; INDIAN FRANKINCENSE; BUTYLENE GLYCOL; CAPRYLYL GLYCOL; CHLORPHENESIN; CITRIC ACID MONOHYDRATE; COCO-CAPRYLATE/CAPRATE; DECYL GLUCOSIDE; DEHYDROACETIC ACID; GLYCYRRHIZINATE DIPOTASSIUM; DISODIUM LAURIMINODIPROPIONATE TOCOPHERYL PHOSPHATES; GLYCERIN; ENOXOLONE; SUNFLOWER OIL; HEXYLENE GLYCOL; HONEY; HYDROGENATED POLYBUTENE (1300 MW); ISODODECANE; LINOLEIC ACID; LINOLENIC ACID; HOLY BASIL LEAF; OLEIC ACID; OLIGOPEPTIDE-10; RICE BRAN; PALMITIC ACID; PANTHENOL; PEG-40 STEARATE; PHENOXYETHANOL; PHENYL TRIMETHICONE; PHENYLPROPANOL; PHOENIX DACTYLIFERA SEED; LECITHIN, SOYBEAN; POLYGLYCERYL-10 STEARATE; DIMETHICONE/VINYL DIMETHICONE CROSSPOLYMER (SOFT PARTICLE); PROPANEDIOL; SODIUM BENZOATE; SODIUM CITRATE, UNSPECIFIED FORM; SODIUM DEHYDROACETATE; STEARIC ACID; MAGNESIUM POTASSIUM ALUMINOSILICATE FLUORIDE; STANNIC OXIDE; TITANIUM DIOXIDE; TOCOPHEROL; WATER; XANTHAN GUM

Drug Facts

Active Ingredients

Allantoin 0.5%, Dimethicone 2%

Purpose

Skin Protectant

Uses

- Temporarily protects and helps relieve chapped or cracked skin.
- Helps protect from the drying effects of wind and cold weather.

Warnings

For external use only.

When using this product

- Do not get in eyes.

Stop use and ask doctor if

- Condition worsens.
- Symptoms last more than 7 days or clear up and occur again within a few days.

Do not use on

- Deep or puncture wounds.
- Animal bites.
- Serious burns.

Keep out of reach of children.

If swallowed, get medical help or contact a Poison Control Center right away.

Directions

After cleansing, apply evenly to face until it blends into skin. Avoid eye area. Do not rinse. Use AM + PM. Reapply as needed.

Inactive ingredients

Annona Cherimola Fruit Extract, Aqua/Eau/Water, Ascorbic Acid, Benzoic Acid, Boswellia Serrata Extract, Butylene Glycol, Caprylyl Glycol, Chlorphenesin, Chlorphenesin, Citric Acid, Coco-Caprylate/Caprate, Decyl Glucoside, Dehydroacetic Acid, Dimethylacrylamide/Acrylic Acid/Polystyrene Ethyl Methacrylate Copolymer, Dipotassium Glycyrrhizate, Disodium Lauriminodipropionate Tocopheryl Phosphates, Glycerin, Glycyrrhetinic Acid, Helianthus Annuus (Sunflower) Seed Oil, Hexylene Glycol, Honey Extract/Mel Extract/Extrait De Miel, Hydrogenated Polyisobutene, Isododecane, Linoleic Acid, Linolenic Acid, Ocimum Sanctum Leaf Extract, Oleic Acid, Oligopeptide-10, Oryza Sativa (Rice) Bran Extract, Palmitic Acid, Panthenol, PEG-40 Stearate, Phenoxyethanol, Phenyl Trimethicone, Phenylpropanol, Phoenix Dactylifera (Date) Seed Extract, Phospholipids, Polyglyceryl-10 Stearate, Polysilicone-11, Propanediol, Sodium Acrylates Copolymer, Sodium Benzoate, Sodium Citrate, Sodium Dehydroacetate, Stearic Acid, Synthetic Fluorphlogopite, Tetrapeptide-16, Tin Oxide, Titanium Dioxide, Titanium Dioxide, Tocopherol, Xanthan Gum.

Questions?

1-888-995-5656

Principal Display Panel – 50 mL Carton Label

RODAN+FIELDS

SOOTHE

Sensitive Skin Treatment

2

50 mL / 1.7 Fl. Oz U.S.

Principal Display Panel – 50 mL Bottle Label

RODAN+FIELDS

SOOTHE

Sensitive Skin Treatment

Skin Protectant Lotion

2